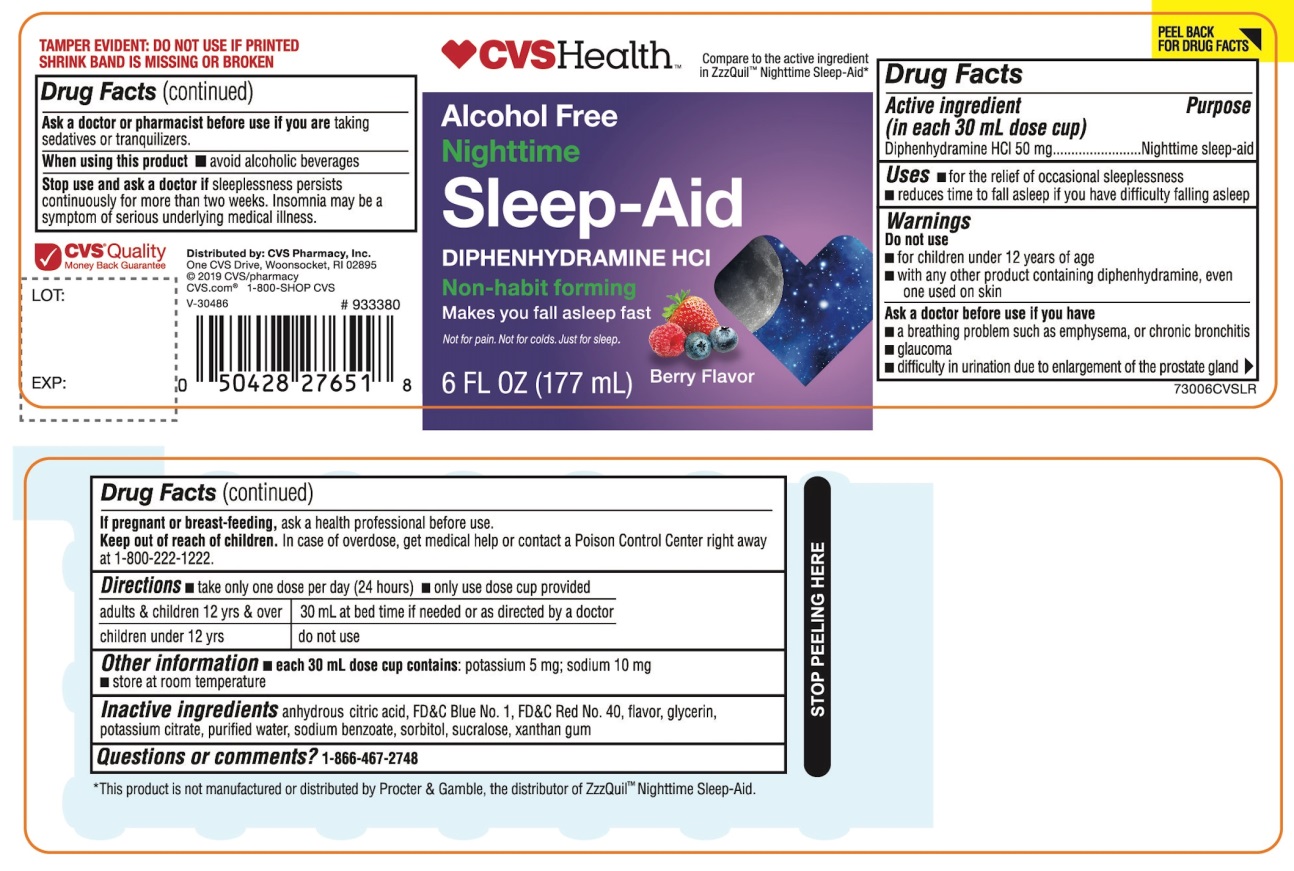 DRUG LABEL: CVS Health Nighttime Sleep-Aid
NDC: 59779-893 | Form: LIQUID
Manufacturer: CVS Pharmacy,Inc.
Category: otc | Type: HUMAN OTC DRUG LABEL
Date: 20251209

ACTIVE INGREDIENTS: DIPHENHYDRAMINE HYDROCHLORIDE 50 mg/30 mL
INACTIVE INGREDIENTS: ANHYDROUS CITRIC ACID; FD&C BLUE NO. 1; FD&C RED NO. 40; GLYCERIN; POTASSIUM CITRATE; WATER; SODIUM BENZOATE; SORBITOL; SUCRALOSE; XANTHAN GUM

CVS Health™Nighttime Sleep-Aid

Drug Facts

Active ingredient (in each 30 mL)

Diphenhydramine HCl 50 mg

Purpose

Nighttime sleep-aid

Uses

- for the relief of occasional sleeplessness
- reduces time to fall asleep if you have difficulty falling asleep

Warnings

Do not use

- for children under 12 years of age
- with any other product containing diphenhydramine, even one used on skin
- with other drugs that cause drowsiness such as antihistamines and nighttime cold/flu products

Ask a doctor before use if you have

- a breathing problem such as asthma, emphysema, or chronic bronchitis
- glaucoma
- difficulty in urination due to enlargement of the prostate gland
- heart disease

Ask a doctor or pharmacist before use if you aretaking sedatives or tranquilizers or any other sleep- aid.

When using this product

- avoid alcoholic beverages and other drugs that cause drowsiness
- drowsiness will occur
- be careful when driving a motor vehicle or operating machinery

Stop use and ask a doctor ifsleeplessness persists continuously for more than two weeks. Insomnia may be a symptom of serious underlying medical illness.

PREGNANCY OR BREAST FEEDING

If pregnant or breast-feeding, ask a health professional before use.

Keep out of reach of children.

Overdose warning:

Taking more than directed can cause serious health problems. In case of overdose, get medical help or contact a Poison Control Center right away at 1-800-222-1222.

Directions

- take only one dose per day (24 hours) – see Overdose warning
- measure with dosing cup provided

adults & children 12yrs & over | One Dose = 30 mL (2 tablespoons) at bed time if needed or as directed by a doctor
Children under 12 yrs | Do not use

Other information

- each 30 mL dose contains: potassium 5 mg; sodium 10 mg
- store at room temperature
- protect from light. Does not meet USP <671>.

Inactive ingredients

anhydrous citric acid, FD&C blue 1, FD&C red 40, flavor, glycerin, potassium citrate, purified water, sodium benzoate, sorbitol, sucralose, xanthan gum.

PRINCIPAL DISPLAY PANEL

CVS Health™

NDC 59779-893-06

Compare to the active ingredient in ZzzQuil® Nighttime Sleep-Aid*

Alcohol Free
Nighttime

Sleep-Aid

DIPHENHYDRAMINE HCl

Non-habit forming

- Not for treating cold or flu

Berry Flavor

Naturally and Artificially Flavored

6 FL OZ (177 mL)

FAILURE TO FOLLOW THESE WARNINGS COULD RESULT IN SERIOUS CONSEQUENCES.

TAMPER EVIDENT: DO NOT USE IF PRINTED SHRINK BAND IS MISSING OR BROKEN

*This product is not manufactured or distributed by Procter & Gamble, the distributor of ZzzQuil®

Distributed by: CVS Pharmacy, Inc.

One CVS Drive, Woonsocket, RI 02895

© 2019CVS/pharmacy

CVS.com®1-800-SHOP CVS

V-30486

CVS® Quality

Money Back Guarantee